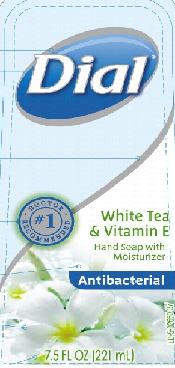 DRUG LABEL: Dial White Tea and Vitamin E Antibacterial Hand Soap
NDC: 54340-802 | Form: SOLUTION
Manufacturer: The Dial Corporation
Category: otc | Type: HUMAN OTC DRUG LABEL
Date: 20110223

ACTIVE INGREDIENTS: TRICLOSAN 0.15 mL/1000 mL
INACTIVE INGREDIENTS: WATER; SODIUM LAURETH SULFATE; DECYL GLUCOSIDE; COCAMIDOPROPYL BETAINE; SODIUM CHLORIDE; COCO MONOETHANOLAMIDE; PEG-120 METHYL GLUCOSE DIOLEATE; POLYETHYLENE GLYCOL 900; GLYCERYL MONOOLEATE; PROPYLENE GLYCOL; GREEN TEA LEAF; ACETATE ION; POLYQUATERNIUM-7 (70/30 ACRYLAMIDE/DADMAC; 1600 KD) ; DMDM HYDANTOIN; EDETATE SODIUM; CITRIC ACID MONOHYDRATE; EXT. D&C VIOLET NO. 2

Drug Facts

Active Ingredient - Triclosan 0.15%

PURPOSE

Antibacterial

INDICATIONS AND USAGE

For hand washing to decrease bacteria on the skin

WARNINGS

For external use only

WHEN USING

Avoid contact with eyes. In case of eye contact, flush with water.

Stop use and ask a doctor if irritation and redness develops.

Keep out of reach of children. If swallowed, get medical help or contact a Poison Control Center right away.

Directions

- Pump into hands, wet as needed
- Lather vigorously for at least 15 seconds
- Wash skin, rinse thoroughly and dry

INACTIVE INGREDIENT

Water, Sodium Laureth Sulfate, Decyl Glucoside, Cocamidopropyl Betaine, Sodium Chloride, Cocamide MEA, Fragrance, PEG-120 Methyl Glucose Dioleate, PEG-18 Glyceryl Oleate/Cocoate, Propylene Glycol, Camellia Sinensis Leaf Extract, Tocopheryl Acetate, Polyquaternium-7, DMDM Hydantoin, Tetrasodium EDTA, Citric Acid, Ext. Violet 2.

Questions? 1-800-258-DIAL (3425)